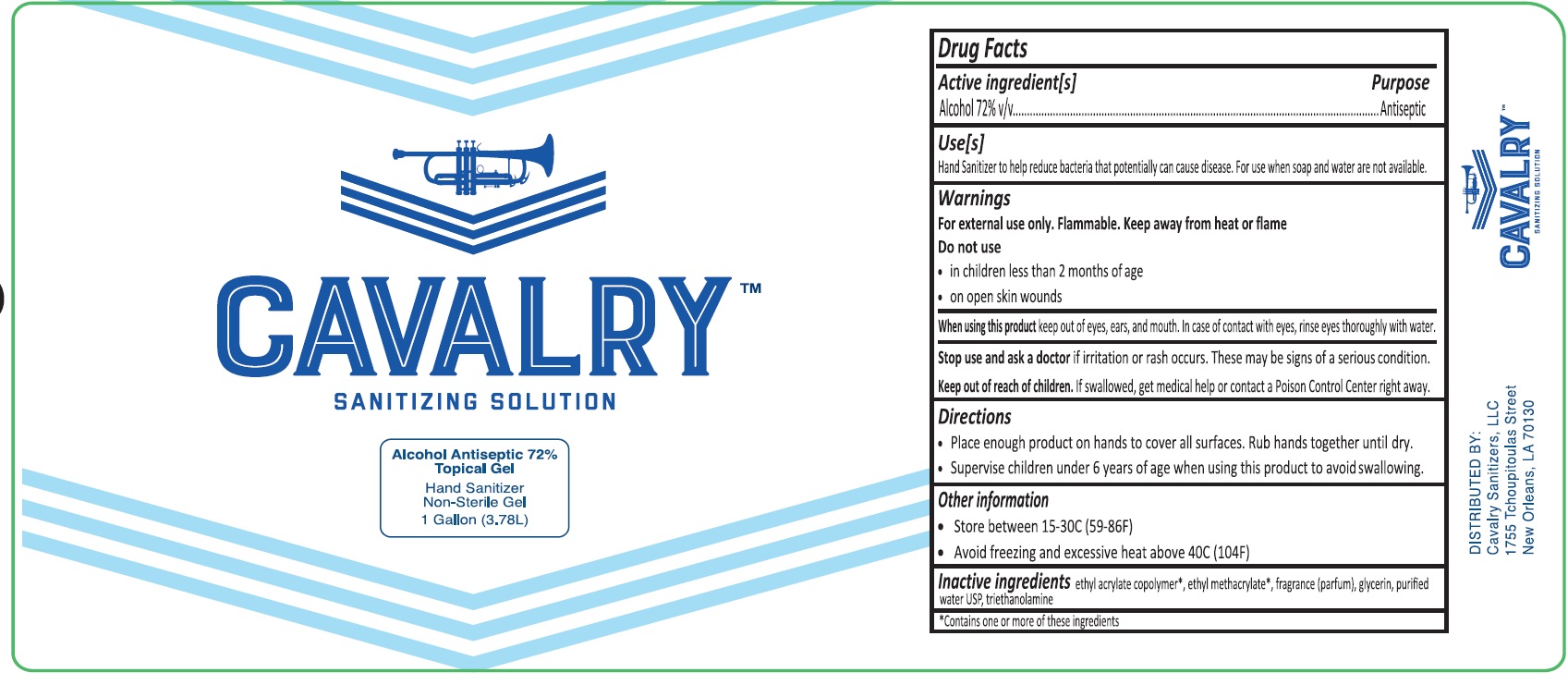 DRUG LABEL: Cavalry
NDC: 75460-072 | Form: SOLUTION
Manufacturer: CAVALRY SANITIZERS, L.L.C.
Category: otc | Type: HUMAN OTC DRUG LABEL
Date: 20200805

ACTIVE INGREDIENTS: ALCOHOL 72 L/100 L
INACTIVE INGREDIENTS: ETHYL METHACRYLATE; GLYCERIN; TROLAMINE; WATER

Active Ingredient(s)

Alcohol 72% v/v

Purpose

Antiseptic

Use

Hand Sanitizer to help reduce bacteria that potentially can cause disease. For use when soap and water are not available.

Warnings

For external use only. Flammable. Keep away from heat or flame

Do not use

- in children less than 2 months of age
- on open skin wounds

When using this product

keep out of eyes, ears, and mouth. In case of contact with eyes, rinse eyes thoroughly with water.

Stop use and ask a doctor if

irritation or rash occurs. These may be signs of a serious condition.

Keep out of reach of children.

If swallowed, get medical help or contact a Poison Control Center right away.

Directions

- Place enough product on hands to cover all surfaces. Rub hands together until dry.
- Supervise children under 6 years of age when using this product to avoid swallowing.

Other information

- Store between 15-30C (59-86F)
- Avoid freezing and excessive heat above 40C (104F)

Inactive ingredients

ethyl acrylate copolymer*, ethyl methacrylate*, fragrance (parfum), glycerin, purified water USP, triethanolamine

* Contains one or more of these ingredients

Principal Display Panel

NDC 75460-072-38

CAVALRYTM

SANITIZING SOLUTION

Alcohol Antiseptic 72% Topical Gel

Hand Sanitizer

Non-Sterile Gel

1 Gallon (3.78 L)